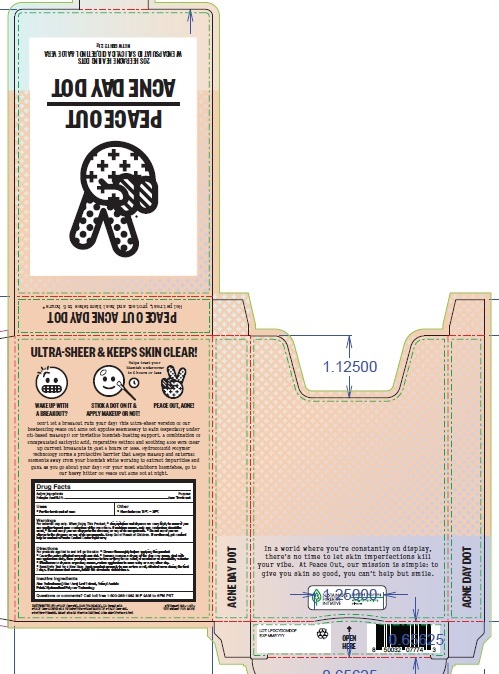 DRUG LABEL: Peace Out Acne Day Dot
NDC: 71494-002 | Form: PATCH
Manufacturer: Peace Out LLC.
Category: otc | Type: HUMAN OTC DRUG LABEL
Date: 20241018

ACTIVE INGREDIENTS: SALICYLIC ACID 0.1575 mg/1 1
INACTIVE INGREDIENTS: VITAMIN A ACETATE; ALOE VERA LEAF

Peace Out Acne Day Dot

Active Ingredients

Salicylic Acid 0.5%

Purpose

Acne Treatment

Uses

- For the treatment of acne

Warnings

For external use only.

When Using This Product

- Skin irritation and dryness is more likely to occur if you use another topical acne medication at the same time. If irritation occurs, only one medication should be used. Do not use if you are allergic to the dressing or any of its components.

Keep Out of Reach of Children

If swallowed, get medical help or contact a Posion Control Center right away.

Directions

For products applied to and left on the skin:

- Cleanse thoroughly before applying this product
- Cover the entire affected area with one dot
- Because excessive drying of the skin may occur, start with one application daily, then gradually increase to two or three times a daily if needed or as directed by a doctor
- If bothersome dryness or peeling occurs, reduce application to once a day or even every other day
- Sensitivity Test for a New User: Apply product sparingly to one or two small affected areas during the first 3 days. If no discomfort occurs, follow the directions stated above.

Other

- Store between 15C - 30C

Inactive Ingredients

Aloe Barbadensis (Aloe Vera) Leaf Extract, Retinyl Acetate

Patch: Hydrocolloid Polymer Technology

Questions of comments?

Call toll free 1-800-268-1962 M-F 9AM to 6PM PST

Company Information

DISTRIBUTED BY: PEACE OUT INC. SAN FRANCISCO, CA 94103 USA